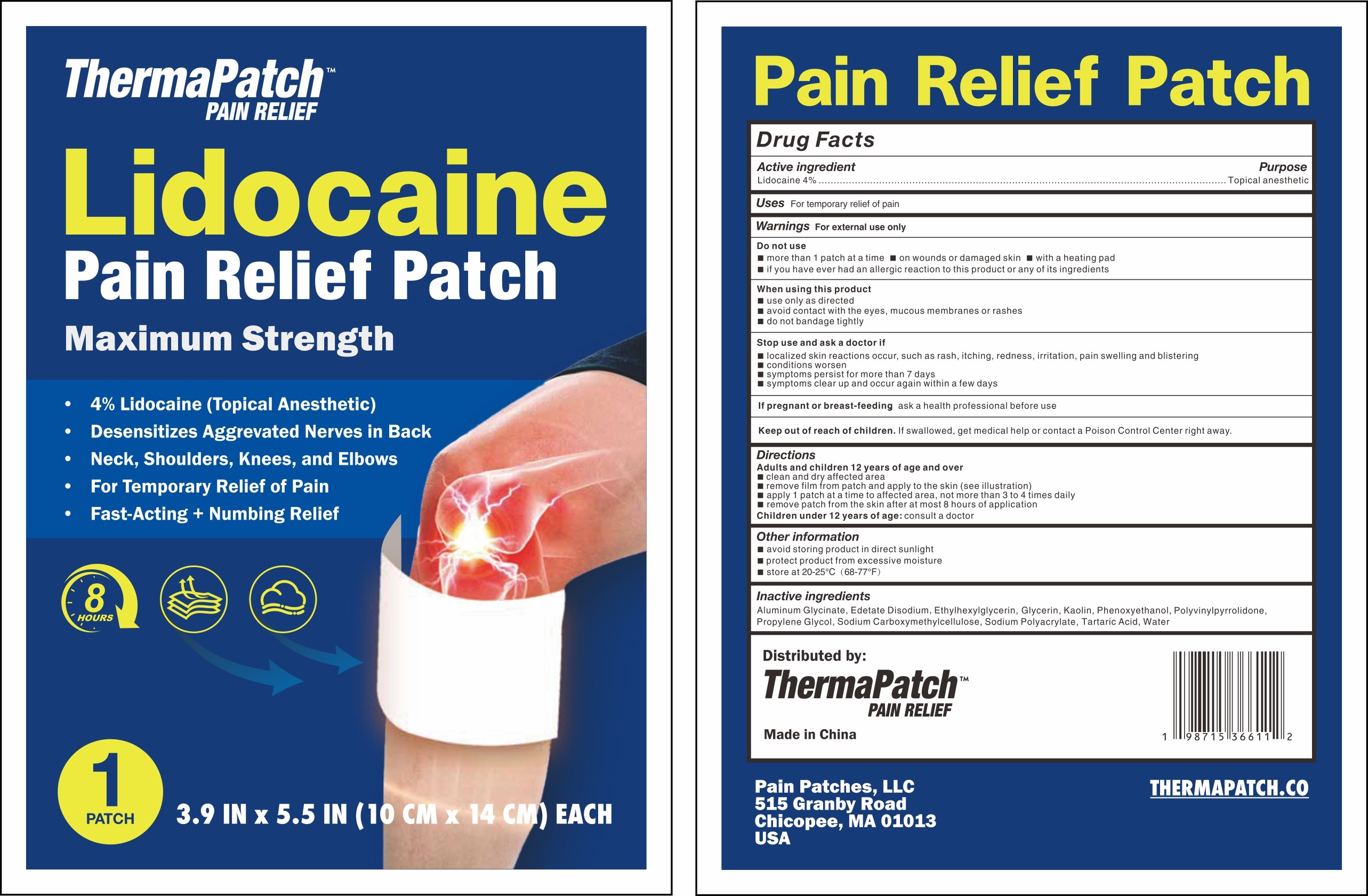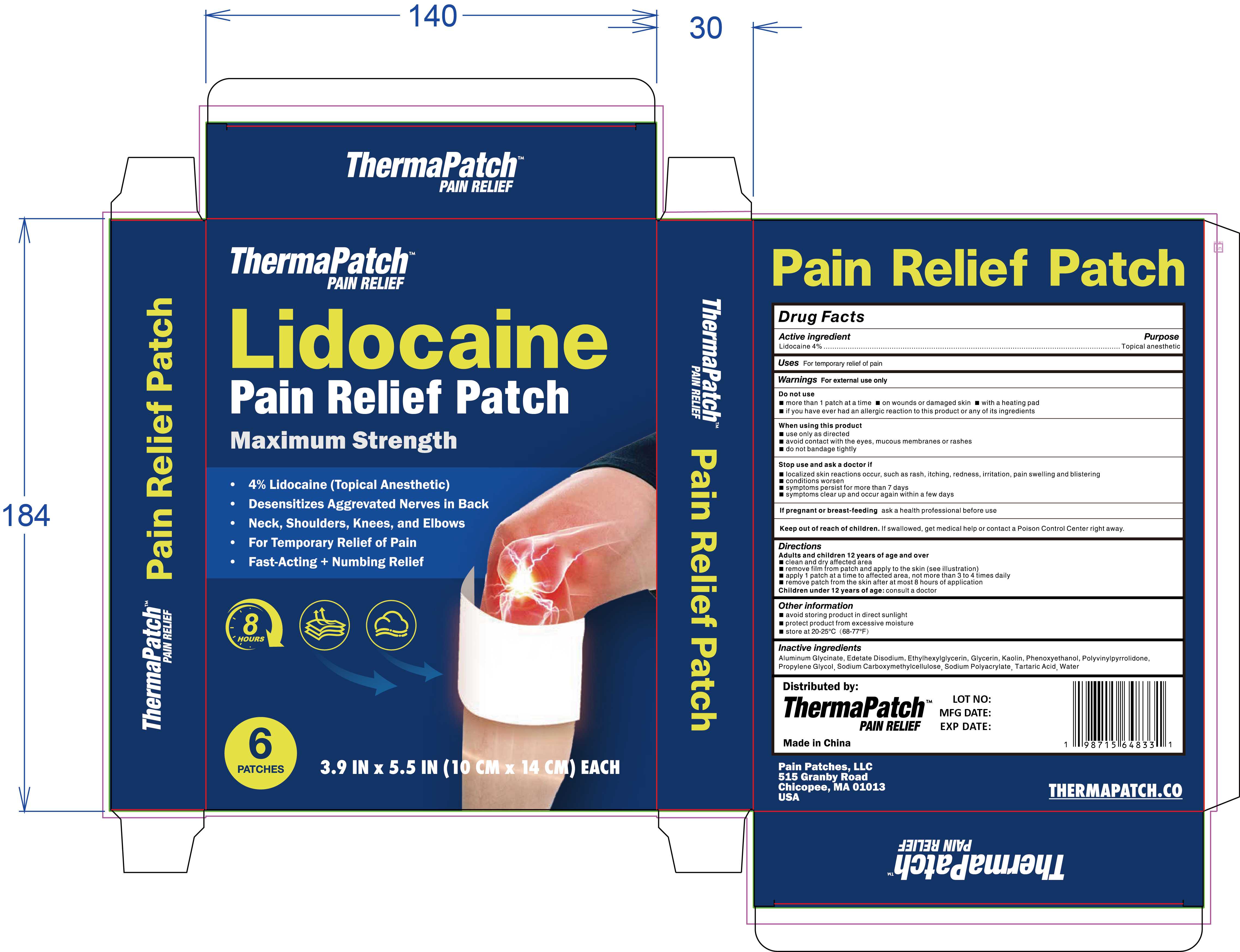 DRUG LABEL: ThermaPatch (TM) Lidocaine Pain Relief Patch
NDC: 83559-006 | Form: PATCH
Manufacturer: Henan Enokon Medical Instrument Co., Ltd.
Category: otc | Type: HUMAN OTC DRUG LABEL
Date: 20241109

ACTIVE INGREDIENTS: LIDOCAINE 4 g/100 1
INACTIVE INGREDIENTS: ALUMINUM GLYCINATE; CARBOXYMETHYLCELLULOSE SODIUM; TARTARIC ACID; PROPYLENE GLYCOL; KAOLIN; WATER; GLYCERIN; PHENOXYETHANOL; SODIUM ACRYLATE; ETHYLHEXYLGLYCERIN; EDETATE DISODIUM; POVIDONE

83559-006

Active Ingredient

Lidocaine 4%

Purpose

Topical anesthetic

Use

For temporary relief of pain

Warnings

For external use only

Do not use

More than 1 patch at a time
On wounds or damaged skin
With a heating pad
If you have ever had an allergic reaction to this product or any of its ingredients

When Using

Use only as directed
Avoid contact with the eyes, mucous membranes or rashes
Do not bandage tightly

Stop Use

Localized skin reactions occur, such as rash, itching, redness, irritation, pain swelling, and blistering
Conditions worsen
Symptoms persist for more than 7 days
Symptoms clear up and occur again within a few days

Ask Doctor

If pregnant or breast-feeding, ask a health professional before use

Keep Oot Of Reach Of Children

If swallowed, get medical help or contact a Poison Control Center right away.

Directions

Adults and children 12 years of age and over:
Clean and dry affected area
Remove film from patch and apply to the skin
Apply 1 patch at a time to affected area, not more than 3 to 4 times daily
Remove patch from the skin after at most 8 hours of application
Children under 12 years of age: consult a doctor

Other information

Avoid storing product in direct sunlight
Protect product from excessive moisture
Store at 20-25°C (68-77°F)

Inactive ingredients

Aluminum Glycinate, Edetate Disodium, Ethylhexylglycerin, Glycerin, Kaolin, Phenoxyethanol, Polyvinylpyrrolidone, Propylene Glycol,
Sodium Carboxymethylcellulose, Sodium Polyacrylate, Tartaric Acid, Water